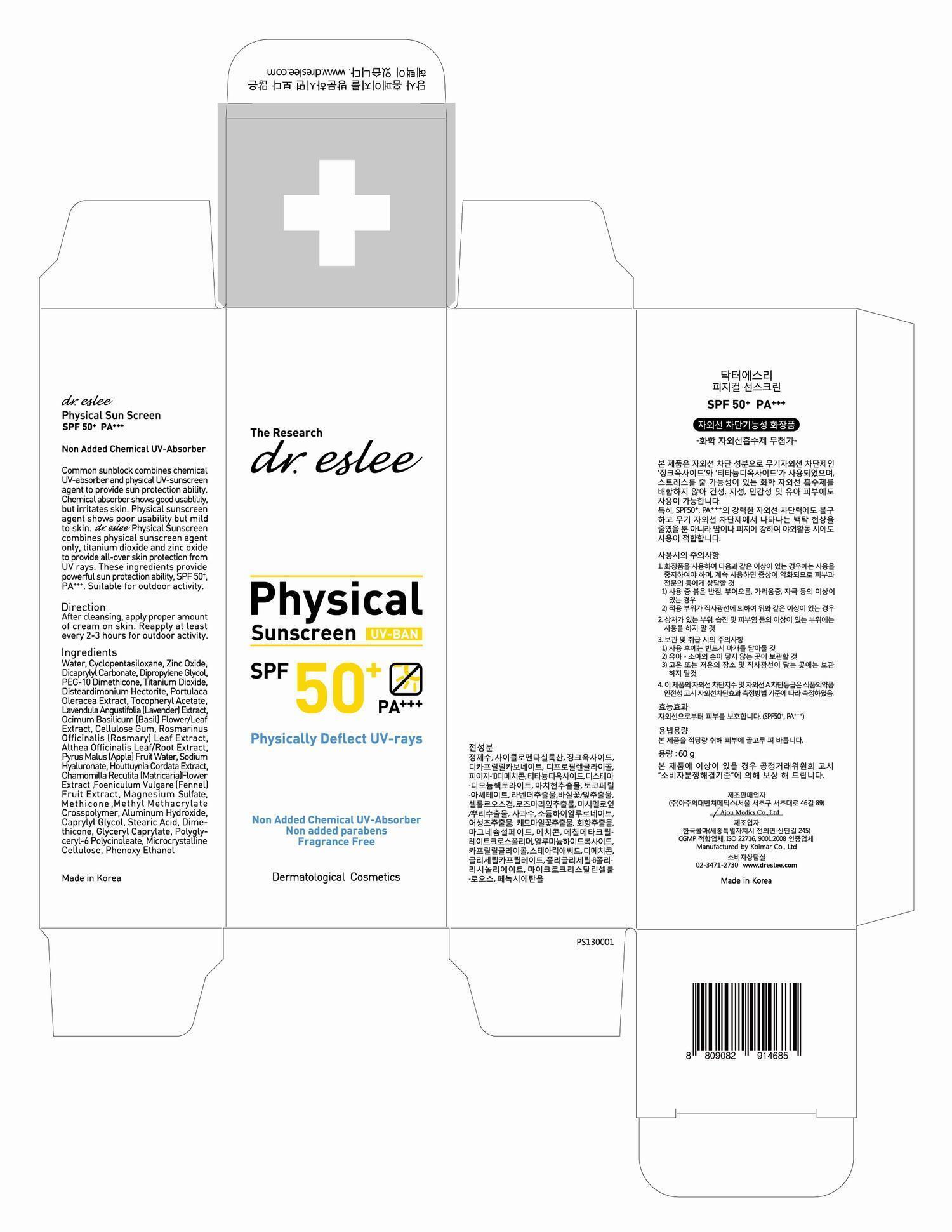 DRUG LABEL: Dr. Eslee Physical Sunscreen
NDC: 82700-0002 | Form: CREAM
Manufacturer: dr.eslee Lab Co., Ltd.
Category: otc | Type: HUMAN OTC DRUG LABEL
Date: 20220514

ACTIVE INGREDIENTS: ZINC OXIDE 0.01248 g/1 g
INACTIVE INGREDIENTS: WATER; CYCLOMETHICONE 5; DICAPRYLYL CARBONATE; DIPROPYLENE GLYCOL; PEG-10 DIMETHICONE (600 CST); TITANIUM DIOXIDE; PORTULACA OLERACEA WHOLE; .ALPHA.-TOCOPHEROL ACETATE; LAVANDULA ANGUSTIFOLIA FLOWER; OCIMUM BASILICUM FLOWERING TOP; CARBOXYMETHYLCELLULOSE SODIUM; ROSEMARY; ALTHAEA OFFICINALIS WHOLE; APPLE; HYALURONATE SODIUM; HOUTTUYNIA CORDATA FLOWERING TOP; MATRICARIA CHAMOMILLA FLOWERING TOP OIL

Drug Facts

ACTIVE INGREDIENT

zinc oxide

INACTIVE INGREDIENT

Water, Cyclopentasiloxane, Dicaprylyl Carbonate, Dipropylene Glycol, PEG-10 Dimethicone, Disteardimonium Hectorite, Portulaca Oleracea Extract, Tocopheryl Acetate, Lavendula Angustifolia (Lavender) Extract, Ocimum Basilicum (Basil) Flower/Leaf Extract, Cellulose Gum, Rosmarinus Officinalis (Rosmary) Leaf Extract, Althea Officinalis Leaf/Root Extract, Pyrus Malus (Apple) Fruit Water, Sodium Hyaluronate, Houttuynia Cordata Extract, Chamomilla Recutita (Matricaria) Flower Extract, Foeniculum Vulgare (Fennel) Fruit Extract, Magnesium Sulfate, Methicone, Methyl Methacrylate Crosspolymer, Aluminum Hydroxide, Caprylyl Glycol, Stearic Acid, Dimethicone, Glyceryl Caprylate, Polyglyceryl-6 Polycinoleate, Microcrystalline Cellulose, Phenoxy Ethanol

PURPOSE

helps to protect from UV-Rays

keep out of reach of the children

INDICATIONS AND USAGE

■ Apply Proper Amount of the cream on skin before sun exposure.
■ Reapply Frequently, every 2 hours for best result.

WARNINGS

■ For external use only.
■ Avoid contact with eyes.
■ Do not swallow. If swallowed, get medical help.
■ Keep out of reach of children.
■ Stop use and ask doctor if rash and irritation develops.

DOSAGE AND ADMINISTRATION

for topical use only